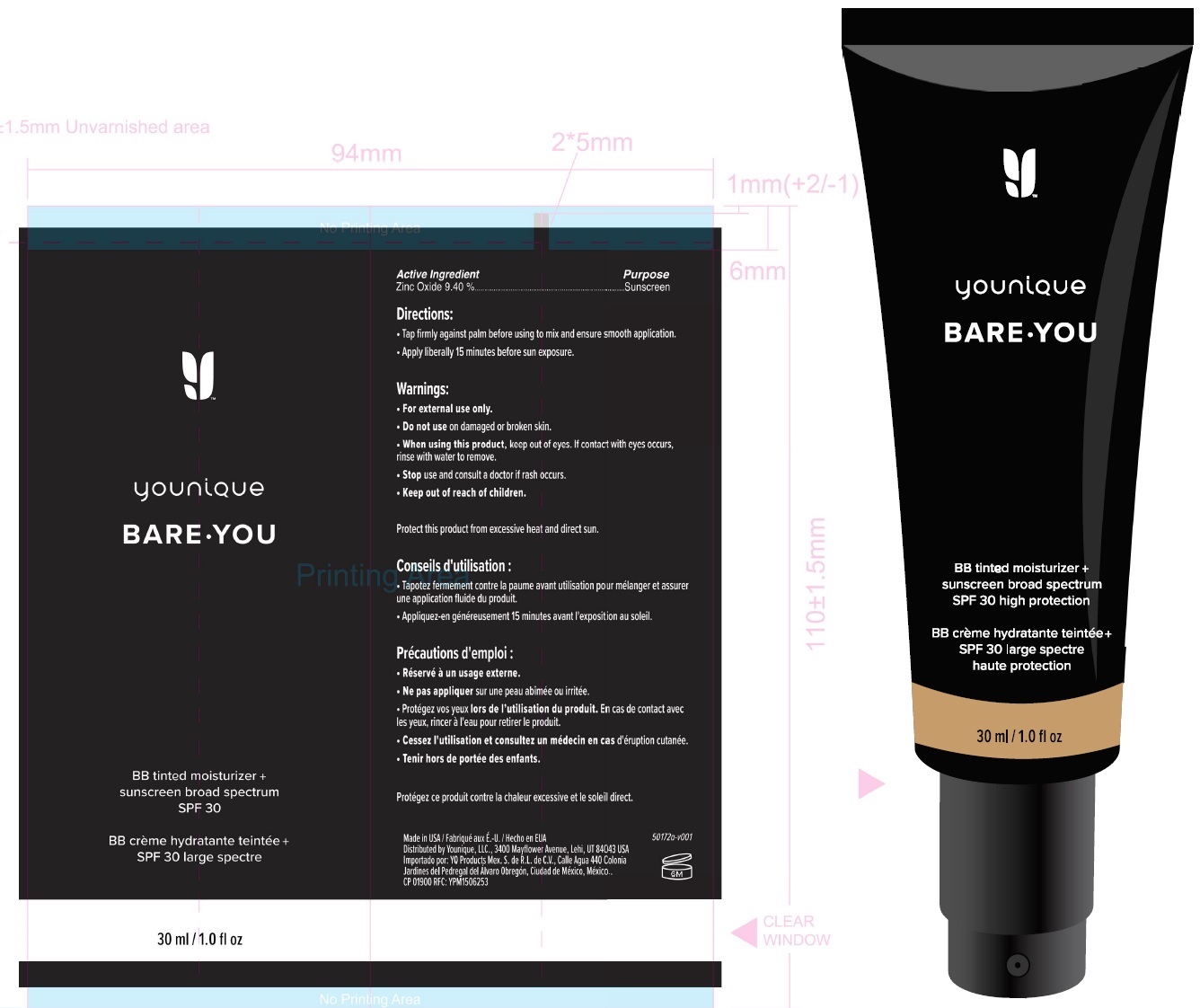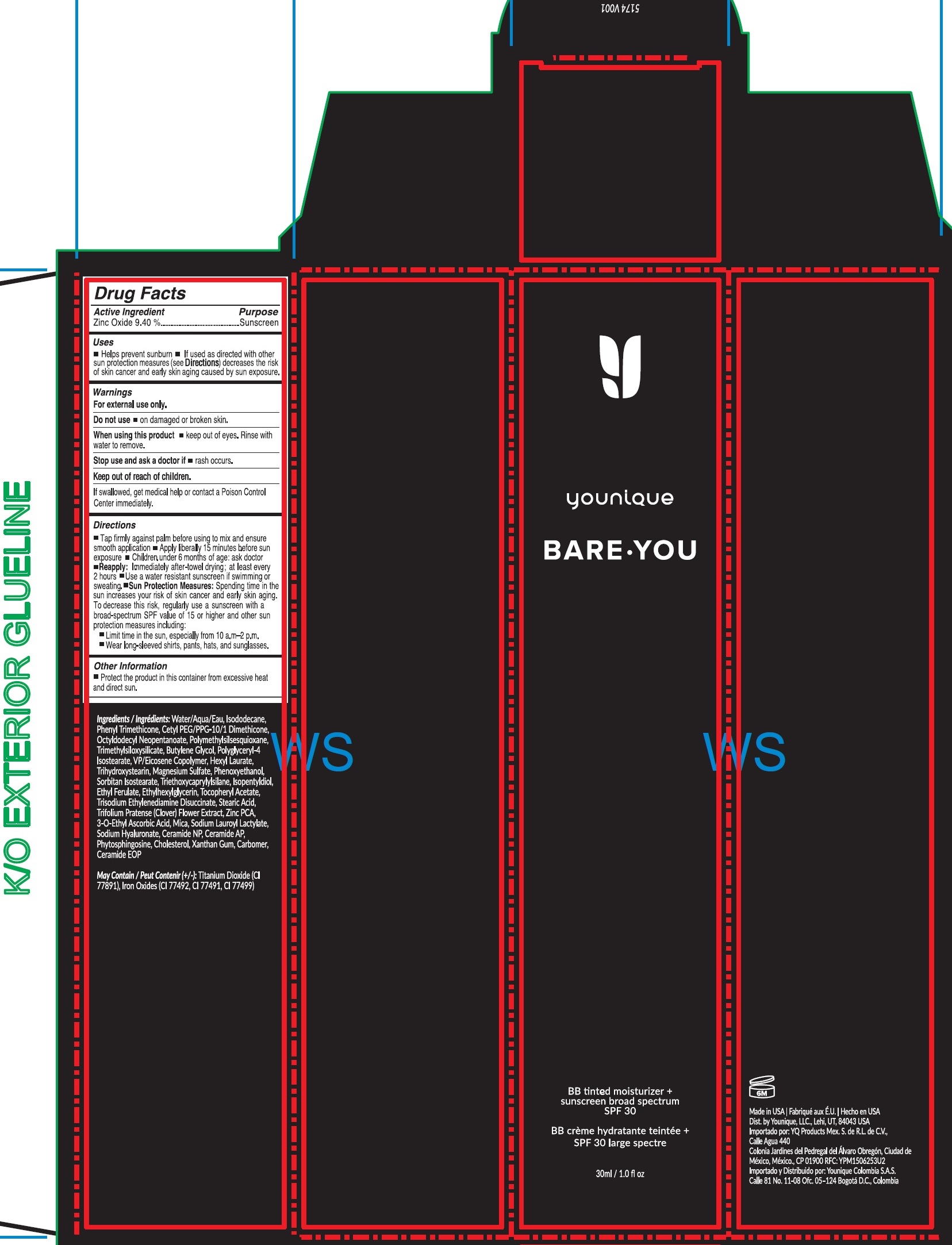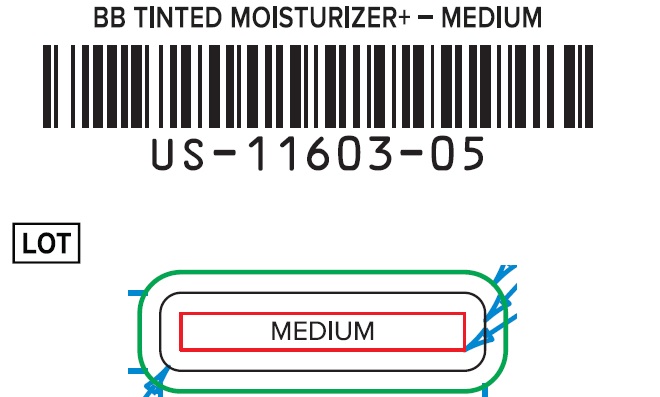 DRUG LABEL: Younique Bare You BB Tinted Moisturizer Sunscreen Broad Spectrum SPF-30 MEDIUM
NDC: 71182-0005 | Form: CREAM
Manufacturer: Younique, LLC
Category: otc | Type: HUMAN OTC DRUG LABEL
Date: 20231130

ACTIVE INGREDIENTS: ZINC OXIDE 94 mg/1 mL
INACTIVE INGREDIENTS: WATER; ISODODECANE; PHENYL TRIMETHICONE; OCTYLDODECYL NEOPENTANOATE; POLYMETHYLSILSESQUIOXANE (4.5 MICRONS); BUTYLENE GLYCOL; POLYGLYCERYL-4 ISOSTEARATE; HEXYL LAURATE; TRIHYDROXYSTEARIN; MAGNESIUM SULFATE, UNSPECIFIED FORM; PHENOXYETHANOL; SORBITAN ISOSTEARATE; TRIETHOXYCAPRYLYLSILANE; ISOPENTYLDIOL; ETHYL FERULATE; ETHYLHEXYLGLYCERIN; .ALPHA.-TOCOPHEROL ACETATE; TRISODIUM ETHYLENEDIAMINE DISUCCINATE; STEARIC ACID; TRIFOLIUM PRATENSE FLOWER; ZINC PIDOLATE; 3-O-ETHYL ASCORBIC ACID; MICA; SODIUM LAUROYL LACTYLATE; HYALURONATE SODIUM; CERAMIDE NP; CERAMIDE AP; PHYTOSPHINGOSINE; CHOLESTEROL; XANTHAN GUM; CARBOMER HOMOPOLYMER, UNSPECIFIED TYPE

Younique Bare You BB Cream Tinted Moisturizer+ Sunscreen Broad Spectrum SPF-30 MEDIUM

Active Ingredient

Zinc Oxide 9.40%

Purpose

Sunscreen

Uses

- Helps prevent sunburn
- If used as directed with other sun protection measures (see) decreases the risk of skin cancer and early skin aging caused by sun exposure. Directions

Warnings

For external use only.

Do not ues

- on damaged or broken skin.

When using this product

- keep out of eyes. Rinse with water to remove.

Stop use and ask a doctor if

- rash occurs.

Keep out of reach of children.

If swallowed, get medical help or contact a Poison Control Center immediately.

Directions

- Tap firmly against palm before using to mix and ensure smooth application
- Apply liberally 15 minutes before sun exposure
- Children under 6 months of age: ask doctor
- : Immediately after-towel drying; at least every 2 hours Reapply
- Use a water resistant sunscreen if swimming or sweating.
- Spending time in the sun increases your risk of skin cancer and early skin aging. To decrease this risk, regulalry use a sunscreen with a broad-spectrum SPF value of 15 or higher and other sun protection measures including: Sun Protection Measures:
- Limit time in the sun, especially from 10 a.m.- 2 p.m.
- Wear long-sleeved shirts, pants, hats, and sunglasses.

Other Information

- Protect the product in this container from excessive heat and direct sun.

Ingredients

Water/Aqua, Isododecane, Phenyl Trimethicone, Cetyl PEG/PPG-10/1 Dimethicone, Octyldodecyl Neopentanoate, Polymethylsilsesquioxane, Trimethylsiloxysilicate, Butylene Glycol, Polyglyceryl-4 Isostearate, VP/Eicosene Copolymer, Hexyl Laurate, Trihydroxystearin, Magnesium Sulfate, Phenoxyethanol, Sorbitan Isostearate, Triethoxycaprylylsilane, Isopentyldiol, Ethyl Ferulate, Ethylhexylglycerin, Tocopheryl Acetate, Trisodium Ethylenediamine Disuccinate, Stearic Acid, Trifolium Pratense (Clover) Flower Extract, Zinc PCA, 3-O-Ethyl Ascorbic Acid, Mica, Sodium Lauroyl Lactylate, Sodium Hyaluronate, Ceramide NP, Ceramide AP, Phytosphingosine, Cholesterol, Xanthan Gum, Carbomer, Ceramide EOP

May Contain (+/-): Titanium Dioxide (CI 77891), Iron Oxides (CI 77492, CI 77491, CI 77499)